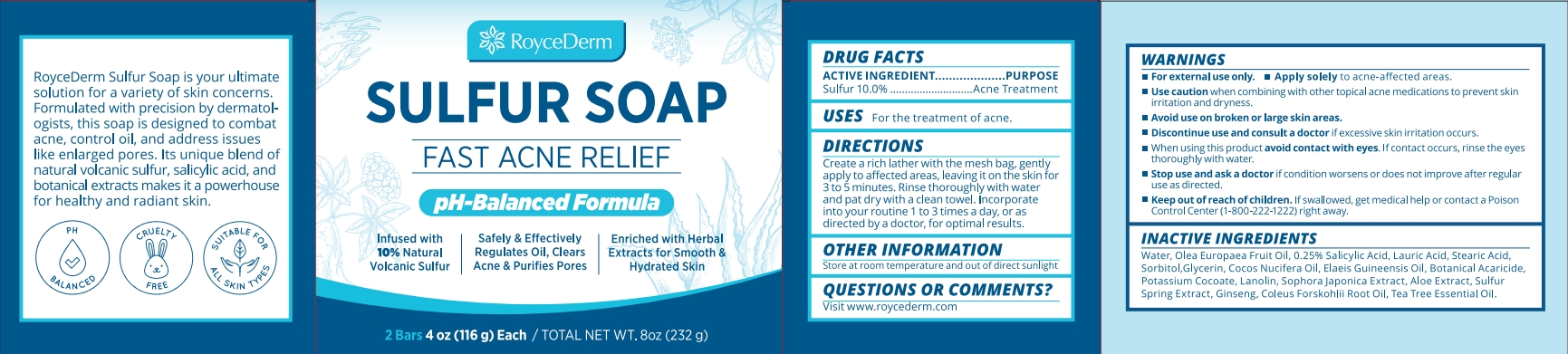 DRUG LABEL: RoyceDerm Sulfur Soap.
NDC: 85424-003 | Form: SOAP
Manufacturer: RoyceDerm LLC
Category: otc | Type: HUMAN OTC DRUG LABEL
Date: 20250718

ACTIVE INGREDIENTS: SULFUR 23.2 g/232 g
INACTIVE INGREDIENTS: WATER; OLEA EUROPAEA (OLIVE) FRUIT OIL; STYPHNOLOBIUM JAPONICUM FLOWER BUD; ALOE; SORBITOL; LAURIC ACID; ELAEIS GUINEENSIS (PALM) OIL; COCOS NUCIFERA (COCONUT) OIL; STEARIC ACID; GLYCERIN; SALICYLIC ACID; COLEUS FORSKOHLII ROOT OIL; POTASSIUM COCOATE; LANOLIN; ASIAN GINSENG; TEA TREE OIL

Initial Drug Listing - RoyceDerm Sulfur Soap Bar

ACTIVE INGREDIENT

Sulfur 10.0%

PURPOSE

Acne Treatment

WHEN USING

For the treatment of acne.

DOSAGE AND ADMINISTRATION

Create a rich lather with the mesh bag, gently apply to affected areas, leaving it on the skin for 3 to 5 minutes. Rinse thoroughly with waterand pat dry with a clean towel. Incorporate into your routine 1 to 3 times a day, or as directed by a doctor, for optimal results.

OTHER SAFETY INFORMATION

Store at room temperature and out of direct sunlight

QUESTIONS

Visit www.roycederm.com

WARNINGS

- For external use only.
- Apply solely to acne-affected areas.Use caution when combining with other topical acne medications to prevent skin
- irritation and dryness.
- Avoid use on broken or large skin areas.
- Discontinue use and consult a doctor ifexcessive skin irritation occurs.
- When using this product avoid contact with eyes. lf contact occurs, rinse the eyes thoroughly with water.

Stop use and ask a doctor if condition worsens or does not improve after regula ruse as directed.

KEEP OUT OF REACH OF CHILDREN

lf swallowed, get medical help or contact a Poison Control center(1-800-222-1222) right away.

INACTIVE INGREDIENT

Water, Olea Europaea Fruit Oil, 0,25% Salicylic Acid, Lauric Acid, Stearic Acid,Sorbitol,Glycerin, Cocos Nucifera Oil, Elaeis Guineensis Oil, Botanical Acaricide.Potassium Cocoate, Lanolin, Sophor ajaponica Extract, Aloe Extract, Sulfur Spring Extract, Ginseng, Coleus Forskohlii Root Oil, Tea Tree Essential Oil.

INDICATIONS AND USAGE

Uses for the treatment of acne